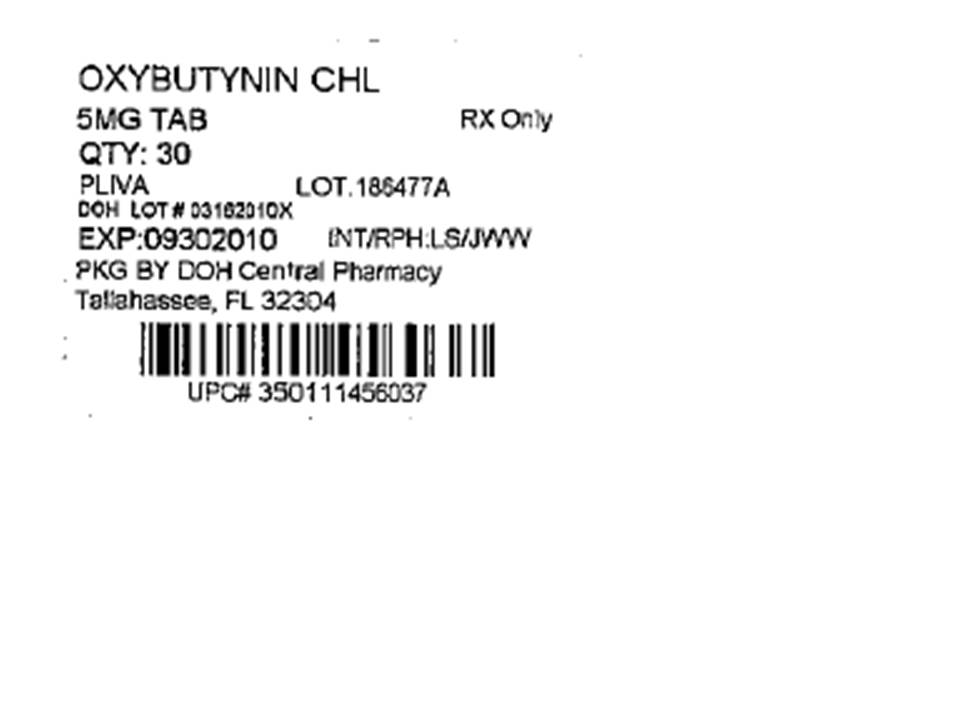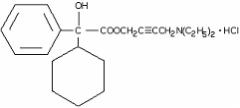 DRUG LABEL: Oxybutynin Chloride
NDC: 53808-0747 | Form: TABLET
Manufacturer: State of Florida DOH Central Pharmacy
Category: prescription | Type: HUMAN PRESCRIPTION DRUG LABEL
Date: 20100607

ACTIVE INGREDIENTS: OXYBUTYNIN CHLORIDE 5 mg/1 1
INACTIVE INGREDIENTS: CALCIUM STEARATE; CELLULOSE, MICROCRYSTALLINE; ANHYDROUS LACTOSE; SODIUM STARCH GLYCOLATE TYPE A POTATO; FD&C BLUE NO. 1

Oxybutynin Chloride Tablets, USP

DESCRIPTION

Oxybutynin chloride is a white crystalline solid, readily soluble in water and acids, but relatively insoluble in alkalis. Chemically, it is the d,i-(racemic) form of 4-diethyl-amino-2-butynyl phenylcyclohexylglycolate hydrochloride with the following formula:

C22H32ClNO3 M.W. 393.9

Each tablet for oral administration contains oxybutynin chloride, USP 5 mg.

Inactive ingredients include calcium stearate, microcrystalline cellulose, anhydrous lactose, sodium starch glycolate and FD&C Blue #1.

CLINICAL PHARMACOLOGY

Oxybutynin chloride exerts direct antispasmodic effect on smooth muscle and inhibits the muscarinic action of acetylcholine on smooth muscle. It exhibits only one-fifth of the anticholinergic activity of atropine on the rabbit detrusor muscle, but four to ten times the antispasmodic activity. No blocking effects occur at skeletal neuromuscular junctions or autonomic ganglia (antinicotinic effects).

Oxybutynin relaxes bladder smooth muscle. In patients with conditions characterized by involuntary bladder contractions, cystometric studies have demonstrated that oxybutynin increases bladder (vesical) capacity, diminishes the frequency of uninhibited contractions of the detrusor muscle, and delays the initial desire to void. Oxybutynin thus decreases urgency and the frequency of both incontinent episodes and voluntary urination.

Oxybutynin chloride was well tolerated in patients administered the drug in controlled studies of 30 days duration and in uncontrolled studies in which some of the patients received the drug for two years. Pharmacokinetic information is not currently available.

INDICATIONS AND USAGE

Oxybutynin chloride tablets are indicated for the relief of symptoms of bladder instability associated with voiding in patients with uninhibited neurogenic or reflex neurogenic bladder (i.e., urgency, frequency, urinary leakage, urge incontinence, dysuria).

CONTRAINDICATIONS

Oxybutynin chloride is contraindicated in patients with untreated angle closure glaucoma and in patients with untreated narrow anterior chamber angles since anticholinergic drugs may aggravate these conditions. It is also contraindicated in partial or complete obstruction of the gastrointestinal tract, paralytic ileus, intestinal atony of the elderly or debilitated patient, megacolon, toxic megacolon complicating ulcerative colitis, severe colitis and myasthenia gravis. It is contraindicated in patients with obstructive uropathy and in patients with unstable cardiovascular status in acute hemorrhage.

Oxybutynin chloride is contraindicated in patients who have demonstrated hypersensitivity to the product.

WARNINGS

Oxybutynin chloride, when administered in the presence of high environmental temperature, can cause heat prostration (fever and heat stroke due to decreased sweating). Diarrhea may be an early symptom of incomplete intestinal obstruction, especially in patients with ileostomy or colostomy. In this instance, treatment with oxybutynin chloride would be inappropriate and possibly harmful.

Oxybutynin chloride may produce drowsiness or blurred vision. The patient should be cautioned regarding activities requiring mental alertness such as operating a motor vehicle or other machinery or performing hazardous work while taking this drug.

Alcohol or other sedative drugs may enhance the drowsiness caused by oxybutynin.

PRECAUTIONS

Oxybutynin chloride should be used with caution in the elderly and in all patients with autonomic neuropathy, hepatic or renal disease. Oxybutynin may aggravate the symptoms of hyperthyroidism, coronary heart disease, congestive heart failure, cardiac arrhythmias, hiatal hernia, tachycardia, hypertension, and prostatic hypertrophy.

Administration of oxybutynin chloride to patients with ulcerative colitis may suppress intestinal motility to the point of producing a paralytic ileus and precipitate or aggravate toxic megacolon, a serious complication of the disease.

Carcinogenesis, Mutagenesis, Impairment of Fertility

A 24-month study in rats at dosages up to approximately 400 times the recommended human dosage showed no evidence of carcinogenicity.

Oxybutynin showed no increase in mutagenic activity when tested in Schizosac-charomyces pompholiciformis, Saccharomyces cerevisiae, and Salmonella typhimurium test symptoms. Reproduction studies in the hamster, rabbit, rat, and mouse have shown no definite evidence of impaired fertility.

Pregnancy

Category B: Reproduction studies in the hamster, rabbit, rat, and mouse have shown no definite evidence of impaired fertility or harm to the animal fetus. The safety of oxybutynin chloride administered to women who are or who may become pregnant has not been established. Therefore, oxybutynin should not be given to pregnant women unless, in the judgment of the physician, the probable clinical benefits outweigh the possible hazards.

Nursing Mothers

It is not known whether this drug is excreted in human milk. Because many drugs are excreted in human milk, caution should be exercised when oxybutynin chloride is administered to a nursing woman.

Pediatric Use

The safety and efficacy of oxybutynin chloride administration have been demonstrated for children 5 years of age and older (see DOSAGE AND ADMINISTRATION). However, as there is insufficient clinical data for children under age 5, oxybutynin is not recommended for this age group.

ADVERSE REACTIONS

Following administration of oxybutynin chloride, the symptoms that can be associated with the use of other anticholinergic drugs may occur:

Cardiovascular: Palpitations, tachycardia, vasodilatation.

Dermatologic: Decreased sweating, rash.

Gastrointestinal/Genitourinary: Constipation, decreased gastrointestinal motility, dry mouth, nausea, urinary hesitance and retention.

Nervous System: Asthenia, dizziness, drowsiness, hallucinations, insomnia, restlessness.

Ophthalmic: Amblyopia, cycloplegia, decreased lacrimation, mydriasis.

Other: Impotence, suppression of lactation.

OVERDOSAGE

The symptoms of overdosage with oxybutynin chloride may be any of those seen with other anticholinergic agents. Symptoms may include signs of central nervous system excitation (e.g., restlessness, tremor, irritability, convulsions, delirium, hallucinations), flushing, fever, nausea, vomiting, tachycardia, hypotension or hypertension, respiratory failure, paralysis, or coma.

In the event of an overdose or exaggerated response, treatment should be symptomatic and supportive. Maintain respiration and induce emesis or perform gastric lavage (emesis is contraindicated in precomatose, convulsive, or psychotic state). Activated charcoal may be administered as well as a cathartic. Physostigmine may be considered to reverse symptoms of anticholinergic intoxication.

Hyperpyrexia may be treated symptomatically with ice bags or other cold applications and alcohol sponges.

DOSAGE AND ADMINISTRATION

Adults: The usual dose is one 5 mg tablet two to three times a day. The maximum recommended dose is one tablet (5 mg) four times a day.

Children over 5 years of age: The usual dose is one 5 mg tablet two times a day. The maximum recommended dose is one tablet (5 mg) three times a day.

HOW SUPPLIED

Oxybutynin Chloride Tablets, USP:

5 mg — Very pale blue, round, scored tablets.

Debossed: PLIVA 456

They are supplied by State of Florida DOH Central Pharmacy as follows:

NDC | Strength | Quantity/Form | Color | Source Prod. Code
53808-0747-1 | 5 mg | 30 Tablets in a Blister Pack | Very pale blue | 50111-456

Dispense in a tight, light-resistant container as defined in the USP.

Store at 20°-25°C (68°-77°F) [See USP Controlled Room Temperature].

Manufactured by:

PLIVA®, Inc.

East Hanover, NJ 07936

This Product was Repackaged By:

State of Florida DOH Central Pharmacy
104-2 Hamilton Park Drive
Tallahassee, FL 32304
United States